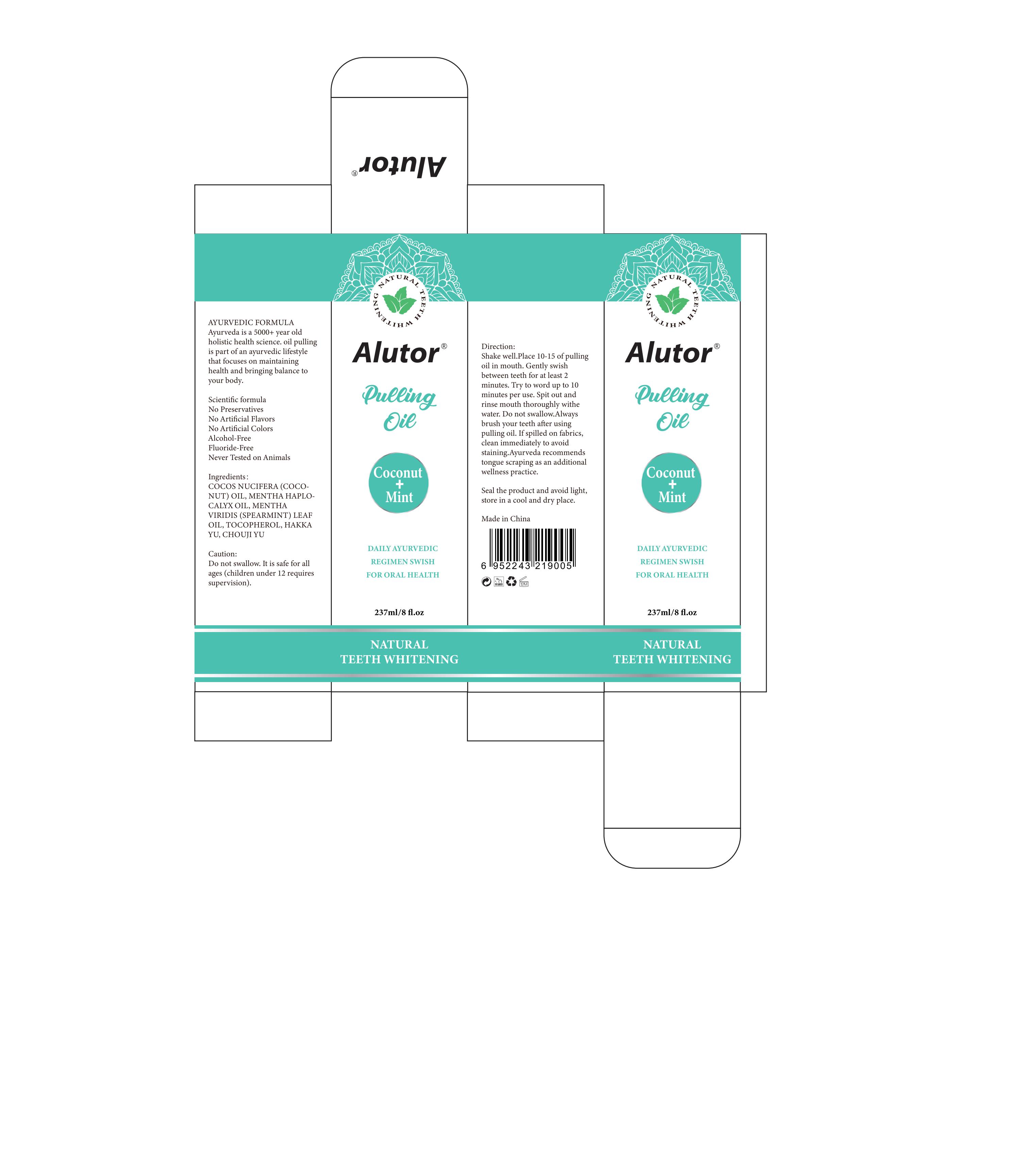 DRUG LABEL: Alutor Pulling Oil
NDC: 83566-154 | Form: OIL
Manufacturer: Guangdong Aimu Biological Technology Co., Ltd
Category: otc | Type: HUMAN OTC DRUG LABEL
Date: 20240716

ACTIVE INGREDIENTS: MENTHA ARVENSIS FLOWER OIL 1 g/100 mL; COCOS NUCIFERA WHOLE 95.2 g/100 mL; MENTHA ARVENSIS LEAF OIL 1 g/100 mL; TOCOPHEROL 2 g/100 mL

Alutor Pulling Oil

Active ingredients

COCOS NUCIFERA(COCONUT) OIL 95.2%
MENTHA HAPLOCALYX OIL 1%
MENTHA VIRIDIS (SPEARMINT) LEAF OIL 1%
TOCOPHEROL 2%

HAKKA YU 0.5%
CHOUJI YU 0.3%

Purpose

oral care

Uses

Shake well. Place 10-15 of pulling oil in mouth. Gently swish between teeth for at least 2 minutes. Try to word up to 10 minutes per use. Spit out and rinse mouth thoroughly withe water. Do not swallow. Always brush your teeth after using pulling oil.

Warnings

For external use only.

Stop use and ask a doctor if

rash occurs.

Do not use

on damaged or broken oral.

When using this product

keep out of eyes. Rinse with water to remove.

Keep out of

reach of children.

Dosage

Place 10-15 of pulling oil in mouth

Inactive ingredients

none